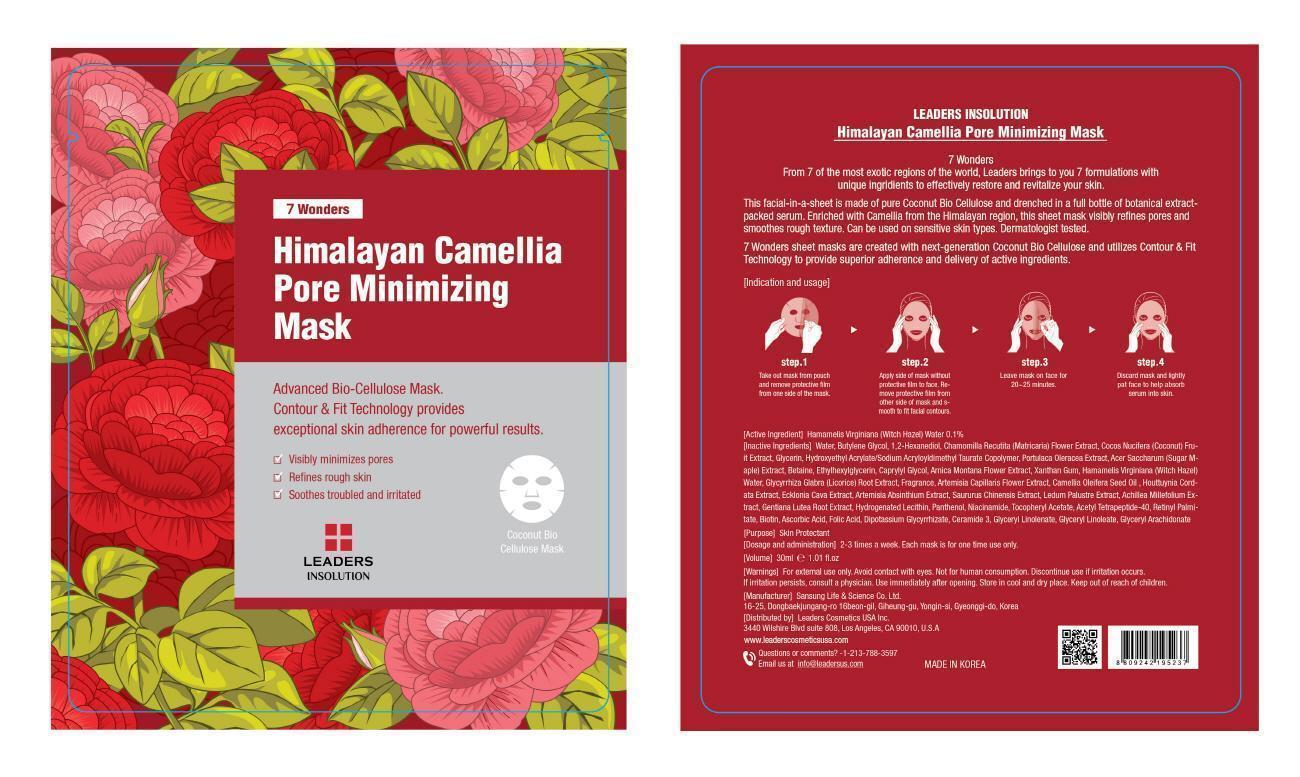 DRUG LABEL: HIMALAYAN CAMELLIA PORE MINIMIZING MASK
NDC: 69424-210 | Form: PATCH
Manufacturer: SANSUNG LIFE & SCIENCE CO., LTD.
Category: otc | Type: HUMAN OTC DRUG LABEL
Date: 20150529

ACTIVE INGREDIENTS: Witch Hazel 0.03 mg/30 mL
INACTIVE INGREDIENTS: Water; Butylene Glycol

ACTIVE INGREDIENT

Active Ingredient: Hamamelis Virginiana (Witch Hazel) Water 0.1%

INACTIVE INGREDIENT

Inactive Ingredients: Water, Butylene Glycol, 1,2-Hexanediol, Chamomilla Recutita (Matricaria) Flower Extract, Cocos Nucifera (Coconut) Fruit Extract, Glycerin, Hydroxyethyl Acrylate/Sodium Acryloyldimethyl Taurate Copolymer, Portulaca Oleracea Extract, Acer Saccharum (Sugar Maple) Extract, Betaine, Ethylhexylglycerin, Caprylyl Glycol, Arnica Montana Flower Extract, Xanthan Gum, Glycyrrhiza Glabra (Licorice) Root Extract, Fragrance, Artemisia Capillaris Flower Extract, Camellia Oleifera Seed Oil, Houttuynia Cordata Extract, Ecklonia Cava Extract, Artemisia Absinthium Extract, Saururus Chinensis Extract, Ledum Palustre Extract, Achillea Millefolium Extract, Gentiana Lutea Root Extract, Hydrogenated Lecithin, Panthenol, Niacinamide, Tocopheryl Acetate, Acetyl Tetrapeptide-40, Retinyl Palmitate, Biotin, Ascorbic Acid, Folic Acid, Dipotassium Glycyrrhizate, Ceramide 3, Glyceryl Linolenate, Glyceryl Linoleate, Glyceryl Arachidonate

PURPOSE

Purpose: Skin Protectant

WARNINGS

Warnings: For external use only. Avoid contact with eyes. Not for human consumption. Discontinue use if irritation occurs. If irritation persists, consult a physician. Use immediately after opening. Store in cool and dry place. Keep out of reach of children.

KEEP OUT OF REACH OF CHILDREN

INDICATIONS & USAGE

Indication and usage: Step 1. Take out mask from pouch and remove protective film from either side of the mask. Step 2. Apply to cleansed face and smooth to fit facial contours. Step 3. Leave mask on face for 20~25 minutes. Step 4. Discard mask and lightly pat face to help absorb serum into skin.

DOSAGE & ADMINISTRATION

Dosage and administration: 2-3 times a week. Each mask is for one time use only.